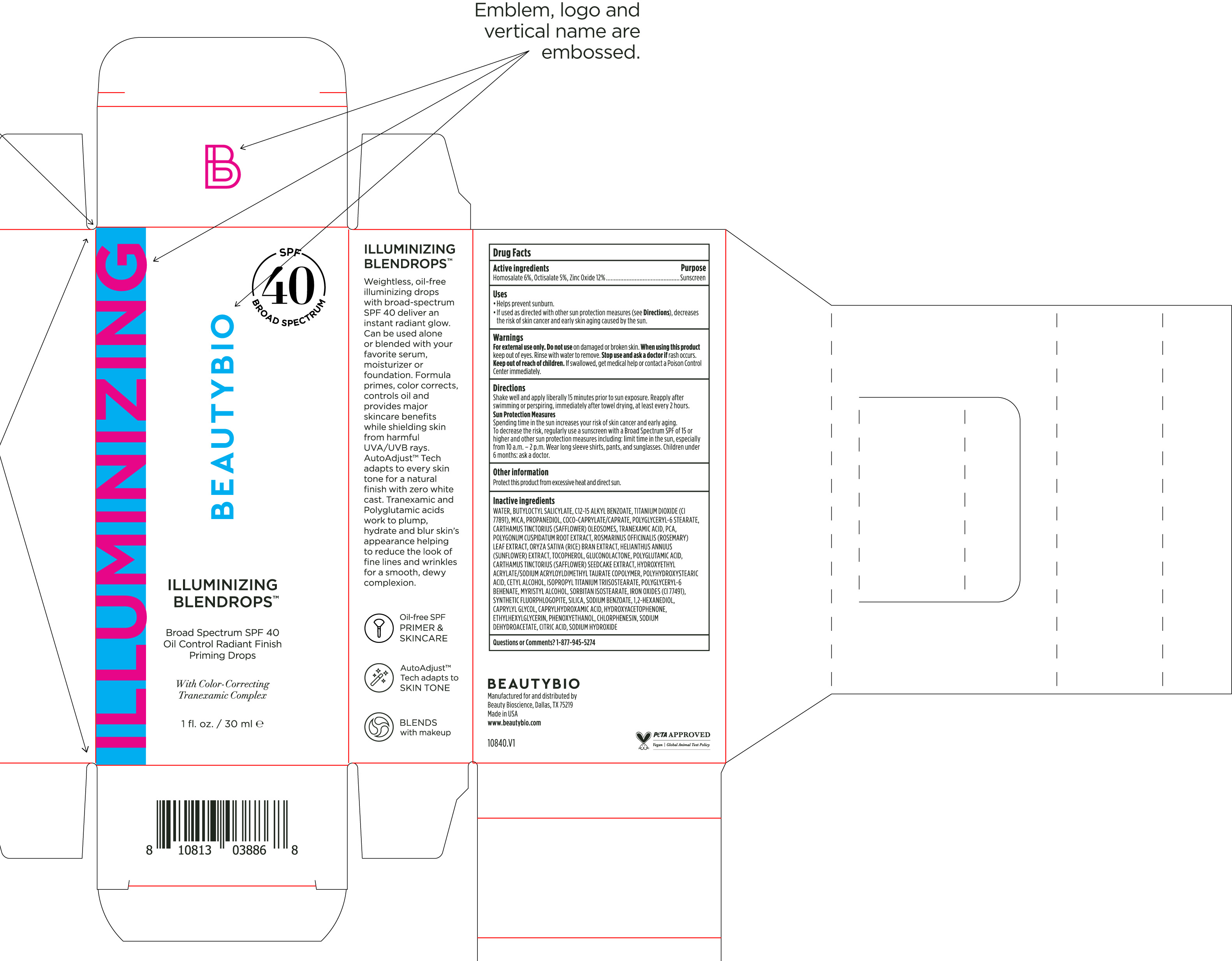 DRUG LABEL: Illuminizing Blendrops Broad Spectrum SPF 40
NDC: 44717-083 | Form: SOLUTION/ DROPS
Manufacturer: Wasatch Product Development, LLC
Category: otc | Type: HUMAN OTC DRUG LABEL
Date: 20251016

ACTIVE INGREDIENTS: OCTISALATE 5 g/100 mL; HOMOSALATE 6 g/100 mL; ZINC OXIDE 12 g/100 mL
INACTIVE INGREDIENTS: PIDOLIC ACID; TOCOPHEROL; GLUCONOLACTONE; CHLORPHENESIN; PROPANEDIOL; CARTHAMUS TINCTORIUS (SAFFLOWER) OLEOSOMES; 1,2-HEXANEDIOL; CAPRYLYL GLYCOL; SODIUM DEHYDROACETATE; SODIUM HYDROXIDE; WATER; ALKYL (C12-15) BENZOATE; ROSEMARY; CARTHAMUS TINCTORIUS SEEDCAKE; HELIANTHUS ANNUUS FLOWERING TOP; HYDROXYETHYL ACRYLATE/SODIUM ACRYLOYLDIMETHYL TAURATE COPOLYMER (45000 MPA.S AT 1%); ISOPROPYL TITANIUM TRIISOSTEARATE; SODIUM BENZOATE; RICE BRAN; MYRISTYL ALCOHOL; POLYGLYCERYL-6 BEHENATE; COCO-CAPRYLATE/CAPRATE; SILICON DIOXIDE; HYDROXYACETOPHENONE; ETHYLHEXYLGLYCERIN; POLYGONUM CUSPIDATUM ROOT; PHENOXYETHANOL; ANHYDROUS CITRIC ACID; BUTYLOCTYL SALICYLATE; CAPRYLHYDROXAMIC ACID; POLYGLYCERYL-6 STEARATE; FERRIC OXIDE RED; TITANIUM DIOXIDE; MICA; TRANEXAMIC ACID; POLYHYDROXYSTEARIC ACID (2300 MW); CETYL ALCOHOL; SORBITAN ISOSTEARATE

Illuminizing Blendrops Broad Spectrum SPF 40

Active Ingredients Purpose

Homosalate 6%, Octisalate 5%, Zinc Oxide 12% ............ Sunscreen

Uses

- Helps prevent sunburn.
- If used as directed with other sun protection measures (see Directions), decreases the risk of skin cancer and early skin aging casued by the sun.

Warnings

Keep out of reach of children. If swallowed, get medical help or contact a Poison Control Center immediately.

Stop use and ask a doctor if rash occurs.

WARNINGS

For external use only. Do not use on damaged or broken skin. When using this product keep out of eyes. Rinse with water to remove.

Directions

Shake well and apply liberally 15 minutes prior to sun exposure. Reapply after swimming or perspiring, immediately after towel drying, at least every 2 hours.

Sun Protection Measures

Spending time in the sun increases your risk of skin cancer and early aging. To decrease the risk, regularyl use a sunscreen with a Broad Spectrum SPF of 15 or higher and other sun protection measures including: limit time in the sun, especially from 10 a.m.- 2p.m. Wear long sleeves shirts, pants, and sunglasses. Children under 6 months: ask a doctor.

Other information

Protect this product from excessive heat and direct sun.

Inactive ingredients

Water, Butyloctyl Salicylate, C12-15 Alkyl Benzoate. Titanium Dioxide (CI 77891), Mica, Propanediol, Coco-Caprylate/Caprate, Polyglyceryl-6 Stearate, Carthamus Tinctorius (Safflower) Oleosomes, Tranexamic Acid, PCA, Polygonum Cuspidatum Root Extract, Rosmarinus Officinalis (Rosemary) Leaf Extract, Oryza Sativa (Rice) Bran Extract, Helianthus Annuus (Sunflower) Extract, Tocopherol, Gluconolactone, Polyglytamic Acid, Carthamus Tinctorius (Safflower) Seedcake Extract, Hydroxyethyl Acryleta/Sodium Acryloyldimethyl Taurate Copolymer, Polyhydroxystearic Acid, Cetyl Alcohol, Isopropryl Titanium Triisostearate, Iron Oxides (CI 77491), Synthetic Fluorphlogopite, Silica, Sodium Benzoate, 1,2-Hexanediol, Caprylyl Glycol, Caprylhydroxamic Acid, Hydroxyacetophenone, Ethylhexylglycerin, Phenoxyethanol, Chlorphenesin, Sodium Dehydroacetate, Citric Acid, Sodium Hydroxide.

Questions or Comments? 1-877-945-5274

PACKAGE LABEL

ILLUMINIZING BLENDROPS

Broad Spectrum SPF 40

Oil Control Radiant Finish Priming Drops

With Color-Correcting Tranexamic Complex

1 fl. oz/30 ml e